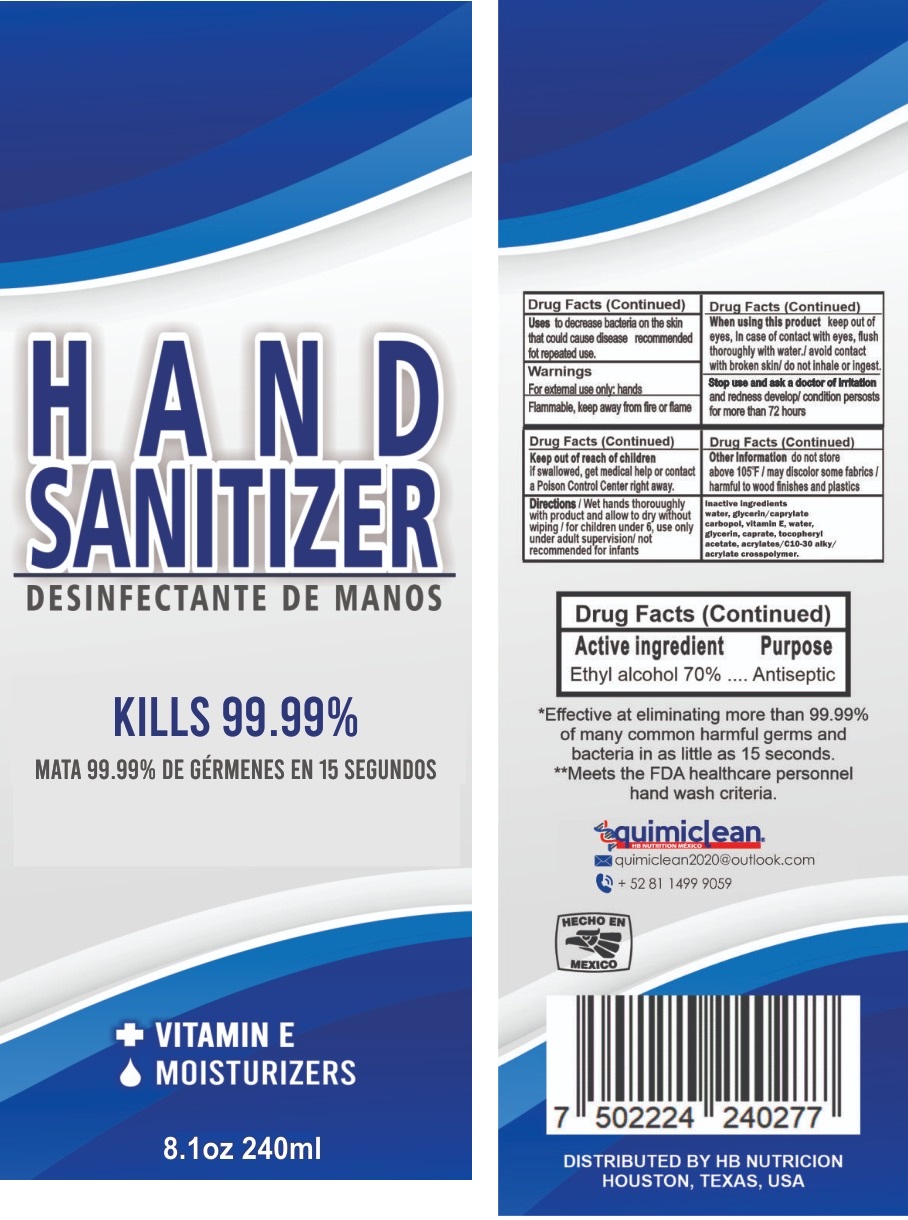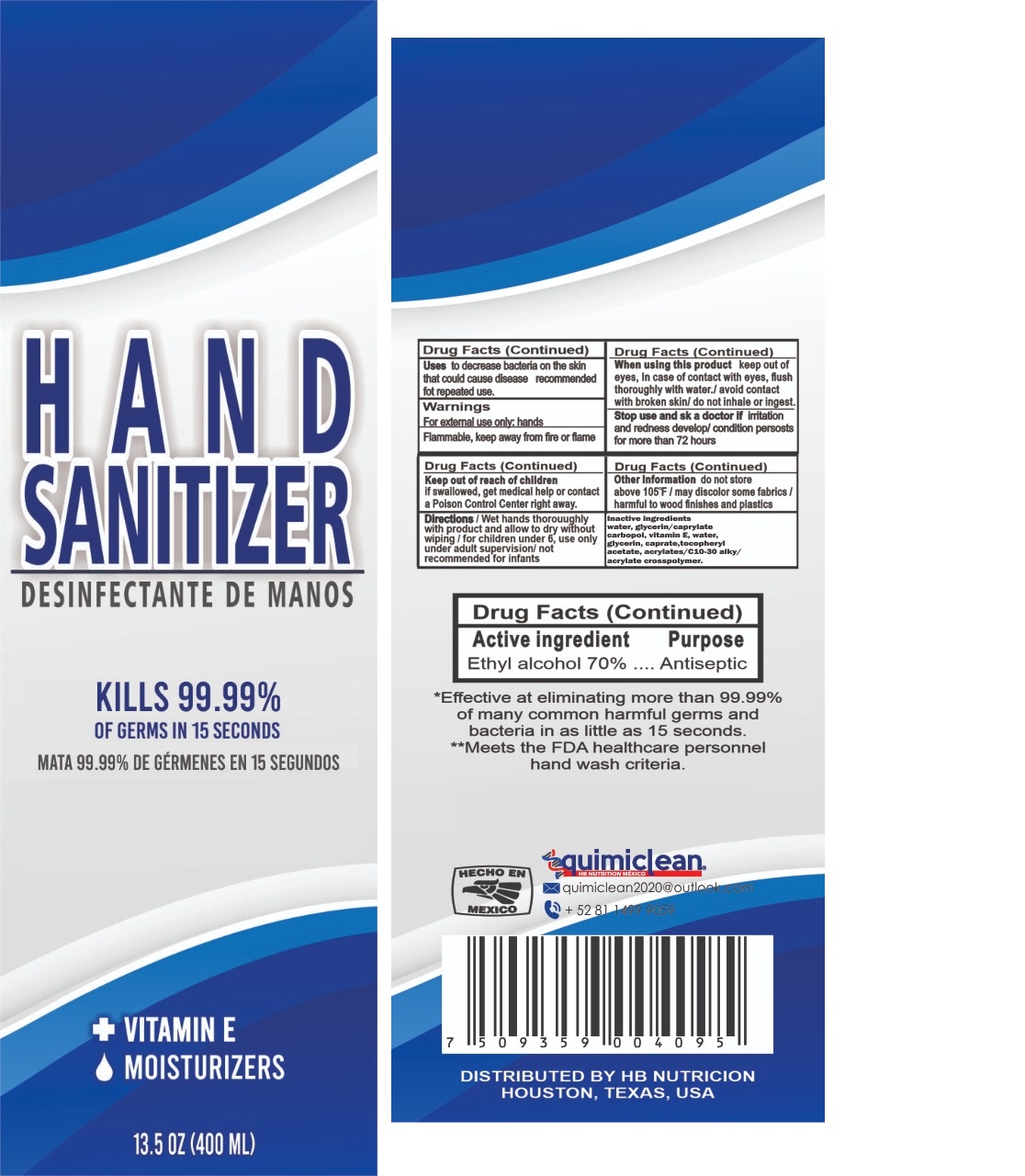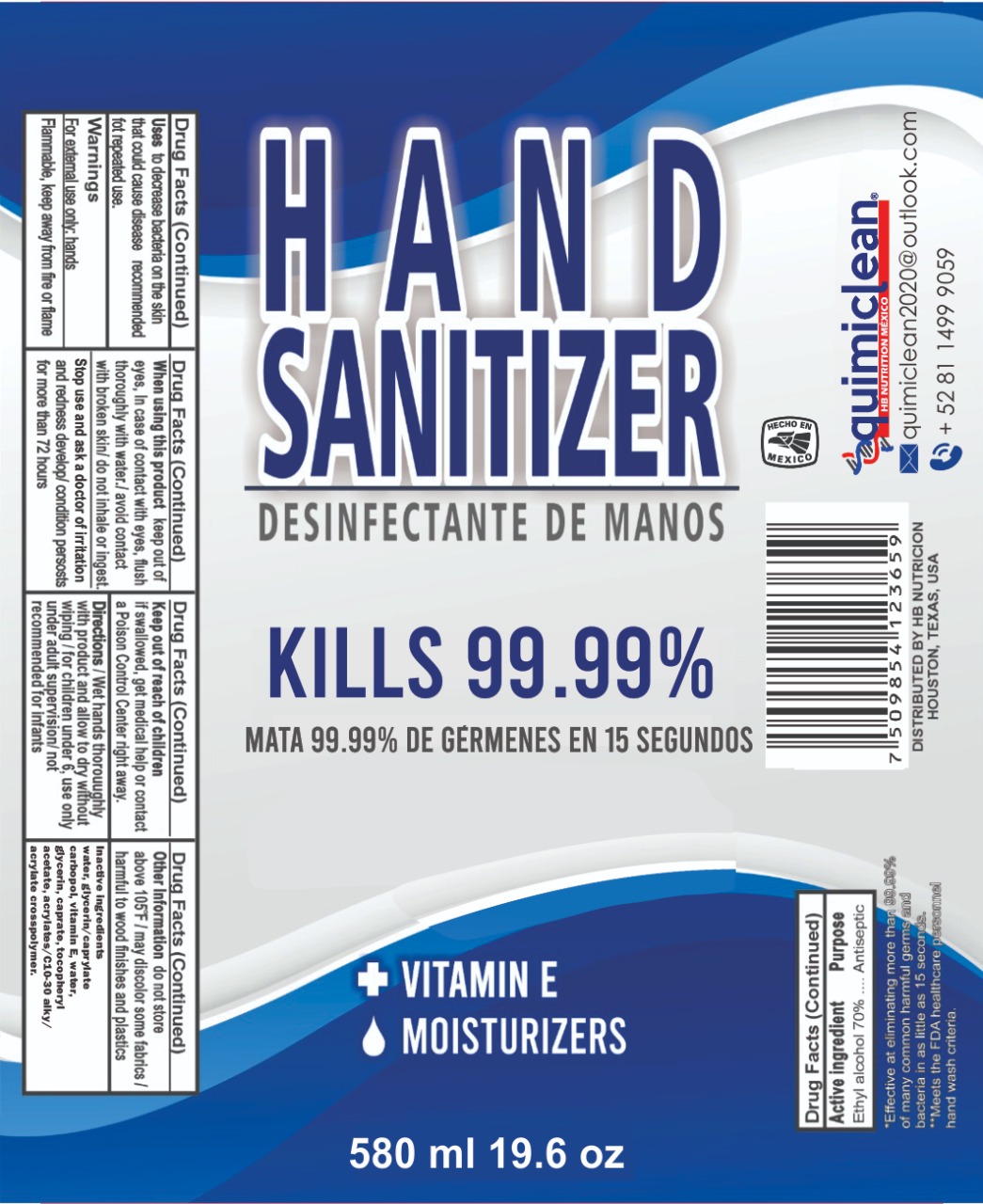 DRUG LABEL: Hand Sanitizer
NDC: 78153-000 | Form: GEL
Manufacturer: Quimi Clean
Category: otc | Type: HUMAN OTC DRUG LABEL
Date: 20200526

ACTIVE INGREDIENTS: ALCOHOL 0.7 mL/1 mL
INACTIVE INGREDIENTS: WATER; GLYCERIN; CAPRYLOYL/CAPROYL METHYL GLUCAMIDE; CARBOMER HOMOPOLYMER, UNSPECIFIED TYPE; .ALPHA.-TOCOPHEROL; .ALPHA.-TOCOPHEROL ACETATE; CARBOMER INTERPOLYMER TYPE A (ALLYL SUCROSE CROSSLINKED)

Hand Sanitizer

Active ingredient

Ethyl alcohol 70%

Purpose

Antiseptic

Uses

to decrease bacteria on the skin that could cause disease recommended for repeated use.

Warnings

For external use only: hands

Flammable, keep away from fire or flame

When using this product

keep out of eyes, In case of contact with eyes, flush thoroughly with water./ avoid contact with broken skin/ do not inhale or ingest.

Stop use and ask a doctor

of irritation and redness develop/ condition persosts for more than 72 hours

Keep out of reach of children

if swallowed, get medical help or contact a Poison Control Center right away.

Directions

Wet hands thorouughly with product and allow to dry without wiping / for children under 6, use only under adult supervision/ not recommended for infacts

Other Information

do not store above 105 F / may discolor some fabrics / harmful to wood finishes and plastics

Inactive Ingredients

Water, glycerin/caprylate carbopol, vitamin E,Water, glycerin, caprate, tocopheryl acetate, acrylates/C10-30 alkyl acrylates crosspolymer